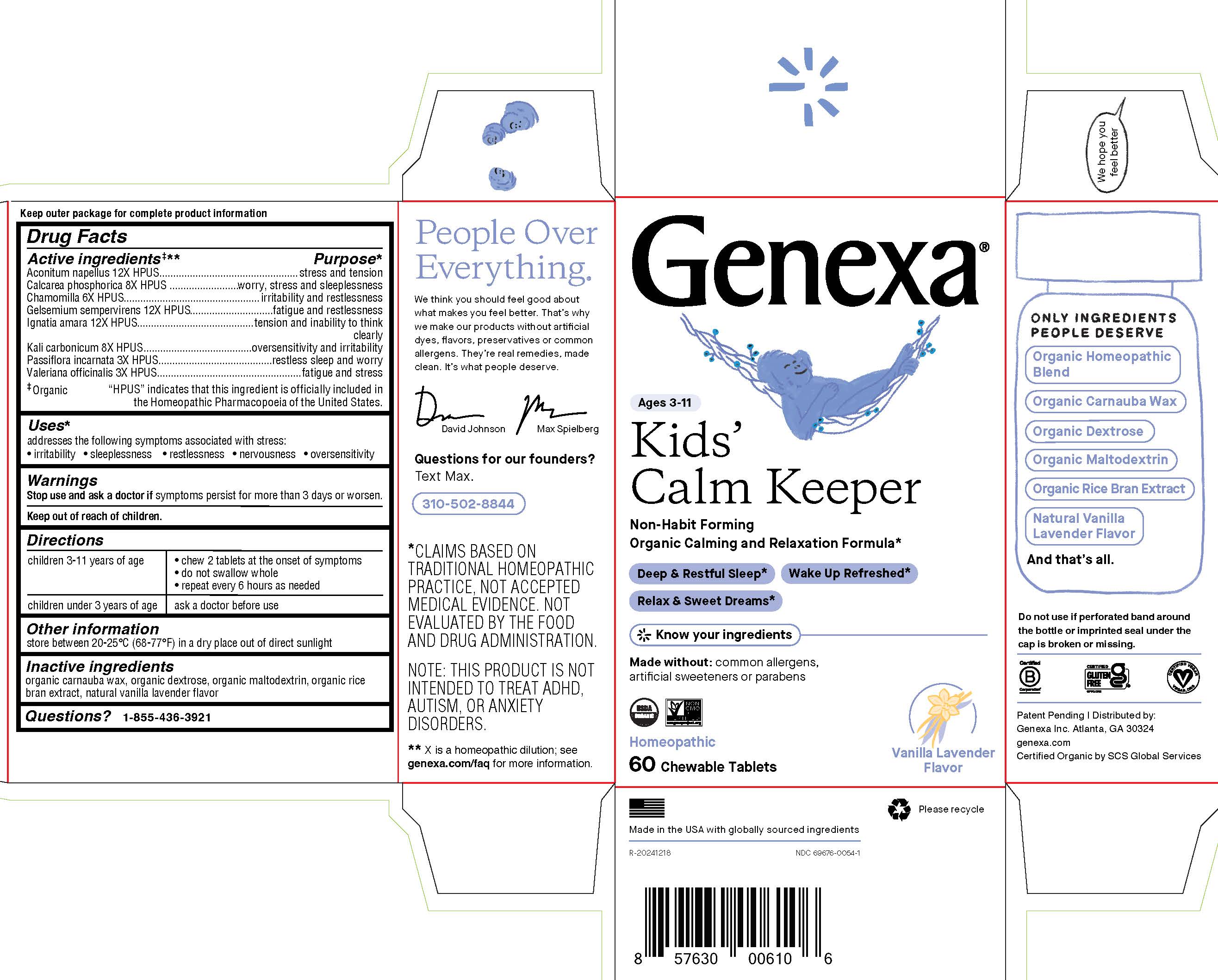 DRUG LABEL: Genexa Kids Calm Keeper
NDC: 69676-0054 | Form: TABLET, CHEWABLE
Manufacturer: Genexa Inc.
Category: homeopathic | Type: HUMAN OTC DRUG LABEL
Date: 20251125

ACTIVE INGREDIENTS: TRIBASIC CALCIUM PHOSPHATE 8 [hp_X]/1 1; MATRICARIA CHAMOMILLA WHOLE 6 [hp_X]/1 1; GELSEMIUM SEMPERVIRENS ROOT 12 [hp_X]/1 1; STRYCHNOS IGNATII SEED 12 [hp_X]/1 1; POTASSIUM CARBONATE 8 [hp_X]/1 1; VALERIAN 3 [hp_X]/1 1; PASSIFLORA INCARNATA FLOWERING TOP 3 [hp_X]/1 1; ACONITUM NAPELLUS 12 [hp_X]/1 1
INACTIVE INGREDIENTS: CARNAUBA WAX; MALTODEXTRIN; RICE BRAN; DEXTROSE

KIDS' CALM KEEPER

Drug Facts

Active ingredients‡**

Aconitum napellus 12X HPUS

Calcarea phosphorica 8X HPUS

Chamomilla 6X HPUS

Gelsemium sempervirens 12X HPUS

Ignatia amara 12X HPUS

Kali carbonicum 8X HPUS

Passiflora incarnata 3X HPUS

Valeriana officinalis 3X HPUS

‡ Organic

"HPUS" indicates that this ingredient is officially included in the Homeopathic Pharmacopoeia of the United States.

Purpose*

stress and tension

worry, stress and sleeplessness

irritability and restlessness

fatigue and restlessness

tension and inability to think clearly

oversensitivity and irritability

restless sleep and worry

fatigue and stress

Uses*

addresses the following symptoms associated with stress:

- irritability
- sleeplessness
- restlessness
- nervousness
- oversensitivity

Warnings

Stop use and ask a doctorif symptoms persist for more than 3 days or worsen.

Keep out of reach of children.

Directions

children 3-11 years of age | - chew 2 tablets at the onset of symptoms - do not swallow whole - repeat every 6 hours as needed
children under 3 years of age | ask a doctor before use

Other information

store between 20-25° C (68-77° F) in a dry place out of direct sunlight

Inactive ingredients

organic carnauba wax, organic dextrose, organic maltodextrin, organic rice bran extract, natural vanilla lavender flavor

Questions?

1-855-436-3921

* CLAIMS BASED ON TRADITIONAL HOMEOPATHIC PRACTICE, NOT ACCEPTED MEDICAL EVIDENCE. NOT EVALUATED BY THE FOOD AND DRUG ADMINISTRATION.

NOTE: THIS PRODUCT IS NOT INTENDED TO TREAT ADHD, AUTISM, OR ANXIETY DISORDERS
** X is a homeopathic dilution: see genexa.com/faq for more information.

Do not use if perforated band around the bottle or imprinted seal under the cap is broken or missing.

Patent Pending | Distributed by:

Genexa Inc. Atlanta, GA 30324

genexa.com

Certified Organic by SCS Global Services

Made in the USA with globally sourced ingredients

NDC 69676-0054-1

PACKAGE LABEL

Genexa®

Ages 3-11

Kids' Calm Keeper

Non-Habit Forming

Organic Calming and Relaxation Formula*

Deep & Restful Sleep*

Wake Up Refreshed*

Relax & Sweet Dreams*

Know your ingredients

Made without: common allergens, artificial sweeteners or parabens

Homeopathic

60 Chewable Tablets

Vanilla Lavender Flavor